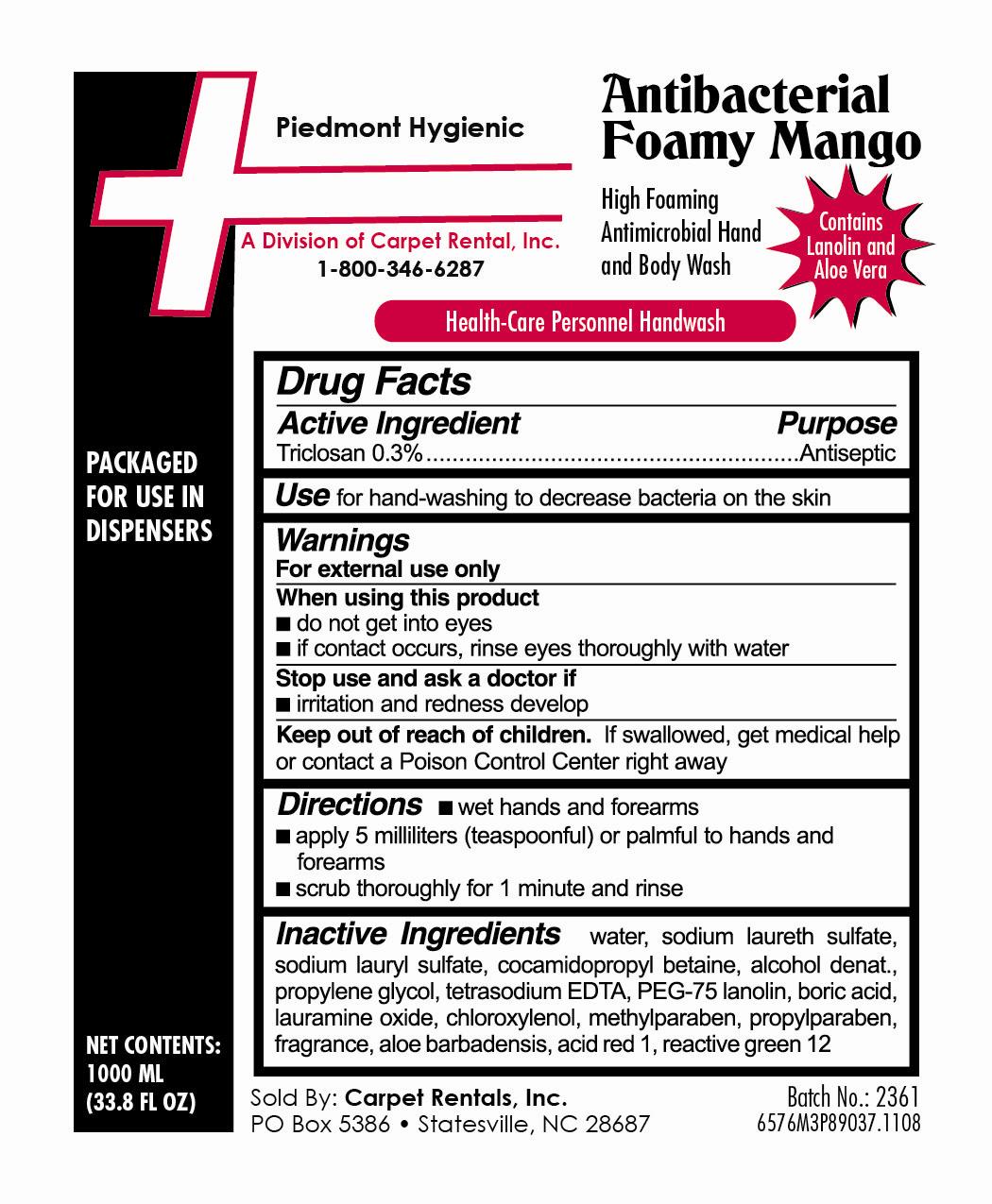 DRUG LABEL: Antibacterial Foamy Mango
NDC: 60456-576 | Form: SOAP
Manufacturer: Carpet Rentals, Inc.
Category: otc | Type: HUMAN OTC DRUG LABEL
Date: 20111103

ACTIVE INGREDIENTS: TRICLOSAN 3.0 mg/1 mL
INACTIVE INGREDIENTS: WATER; PROPYLENE GLYCOL; SODIUM LAURETH SULFATE; COCAMIDOPROPYL BETAINE; BORIC ACID; ALCOHOL; CHLOROXYLENOL; ALOE VERA LEAF; PROPYLPARABEN; METHYLPARABEN; SODIUM LAURYL SULFATE; LAURAMINE OXIDE; PEG-75 LANOLIN; EDETATE SODIUM

Antibacterial Foamy Mango 6576 Drug Facts and Label

Drug Facts Box OTC-Active Ingredient Section

Triclosan 0.3%

Drug Facts Box OTC-Purpose Section

Antiseptic

Drug Facts Box OTC-Indications & Usage Section

for hand-washing to decrease bacteria on the skin

Drug Facts Box OTC-Warnings Section

For external use only

Drug Facts Box OTC-When Using Section

do not get into eyes

if contact occurs, rinse eyes thoroughly with water

Drug Facts Box OTC-Stop Use Section

irritation and redness develop

Drug Facts Box OTC-Keep Out of Reach of Children Section

if swallowed, get medical help or contact a Poison Control Center right away

Drug Facts Box OTC-Dosage & Administration Section

wet hands and forearms

apply 5 milliliters (teaspoonful) or palmful to hands and forearms

scrub thoroughly for 1 minute and rinse

Drug Facts Box OTC-Inactive Ingredient Section

water, sodium laureth sulfate, sodium lauryl sulfate, cocamidopropyl betaine, alcohol denat., propylene glycol, tetrasodium EDTA, PEG-75 lanolin, boric acid, lauramine oxide, chloroxylenol, methylparaben, propylparaben, fragrance, aloe barbadensis, acid red 1, reactive green 12

Antibacterial Foamy Mango 6576 1000ml

6576M3P89037.jpg Antibacterial Foamy Mango 1000 ml